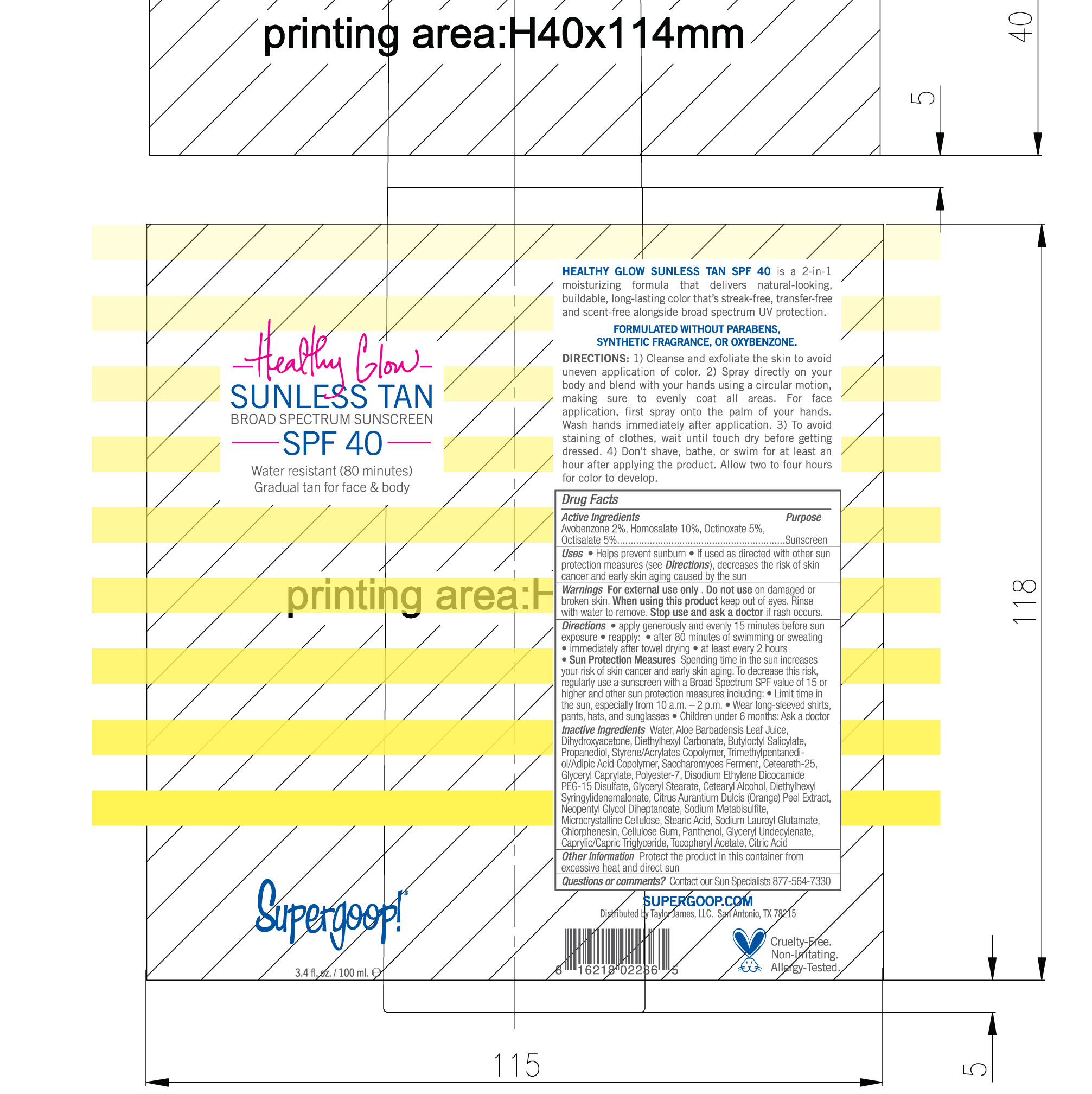 DRUG LABEL: Healthy Glow Sunless Tan Broad Spectrum SPF 40
NDC: 75936-143 | Form: LOTION
Manufacturer: Supergoop LLC
Category: otc | Type: HUMAN OTC DRUG LABEL
Date: 20230408

ACTIVE INGREDIENTS: AVOBENZONE 2 g/100 mL; HOMOSALATE 10 g/100 mL; OCTINOXATE 5 g/100 mL; OCTISALATE 5 g/100 mL
INACTIVE INGREDIENTS: MEDIUM-CHAIN TRIGLYCERIDES; ALOE VERA LEAF; DIETHYLHEXYL SYRINGYLIDENEMALONATE; SODIUM METABISULFITE; MICROCRYSTALLINE CELLULOSE; POLYESTER-7; DISODIUM ETHYLENE DICOCAMIDE PEG-15 DISULFATE; GLYCERYL MONOSTEARATE; CHLORPHENESIN; CARBOXYMETHYLCELLULOSE SODIUM, UNSPECIFIED FORM; PANTHENOL; GLYCERYL 1-UNDECYLENATE; CITRIC ACID MONOHYDRATE; TRIMETHYLPENTANEDIOL/ADIPIC ACID/GLYCERIN CROSSPOLYMER (25000 MPA.S); STEARIC ACID; SODIUM LAUROYL GLUTAMATE; ORANGE PEEL; NEOPENTYL GLYCOL DIHEPTANOATE; .ALPHA.-TOCOPHEROL ACETATE; BUTYLOCTYL SALICYLATE; CETEARETH-25; DIHYDROXYACETONE; DIETHYLHEXYL CARBONATE; PROPANEDIOL; GLYCERYL CAPRYLATE; CETOSTEARYL ALCOHOL

Supergoop (as PLD) - Healthy Glow Sunless Tan Broad Spectrum SPF 40

Active ingredients Purpose

Avobenzone 2% Sunscreen

Homosalate 10%

Octinoxate 5%

Octisalate 5%

Uses

- Helps prevent sunburn
- If used as directed with other sun protection measures (see Directions), decreases the risk of skin cancer and early skin aging caused by the sun

Stop use and ask a doctor if rash occurs.

Warnings

For external use only. Do not use on damaged or broken skin. When using this product keep out of eyes. Rinse with water to remove.

KEEP OUT OF REACH OF CHILDREN.

Directions

- apply generously and evenly 15 minutes before sun exposure

reapply:

- after 80 minutes of swimming or sweating
- immediately after towel drying
- at least every 2 hours
- Sun Protection Measures Spending time in the sun increases your risk of skin cancer and eartl skin aging. To decrease this risk, regularly use a sunscreen with a Broad Spectrum value of 15 or higher and other sun protection measures including:
- Limit time in the sun, especially from 10 a.m.-2 p.m.
- Wear long-sleeved shirts, pants, hats, and sunglasses
- Children under 6 months: ask a doctor

INACTIVE INGREDIENT

Inactive Ingredients: Water, Aloe Barbadensis Leaf Juice, Dihydroxyacetone, Diethylhexyl Carbonate, Butyloctyl Salicylate, Propanediol, Styrene/Acrylates Copolymer, Trimethylpentanediol/adipic Acid Copolymer, Saccharomyces, Ferment, Ceteareth-25, Glyceryl Caprylate, Polyester-7, Disodium Ethylene Diocamide PEG-15 Disulfate, Glyceryl Stearate, Cetearyl Alcohol, Diethylhexyl Syringylidenemalonate, Citrus Aurantium Dulcis (orange) Peel extract, Neopentyl Glycol Diheptanoate, Sodium Metabisulfsite, Microcrystalline Cellulose, Stearic Acid, Sodium Lauryl Glutamate, Chlorphenesin, Cellulose Gum, Panthenol, Glyceryl Undecylenate, Caprylic/Capric Triglyceride, Tocopheryl Acetate, Citric Acid

PACKAGE LABEL

Healthy Glow

Sunless Tan Broad Spectrum SPF 40

Supergoop!

3.4 fl. oz./ 100 mL